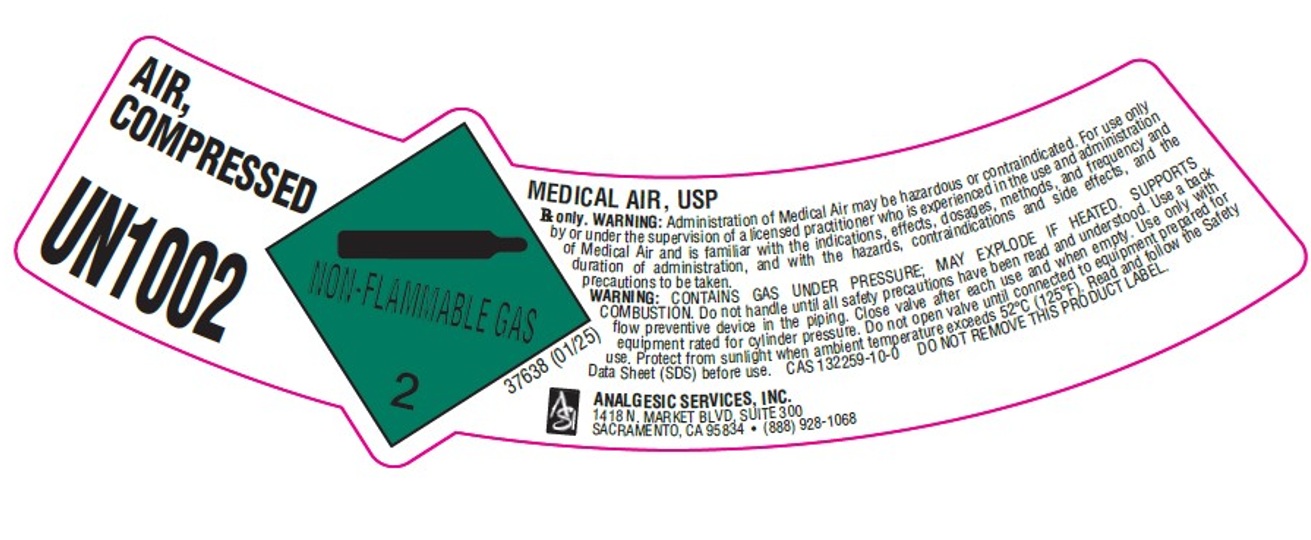 DRUG LABEL: Air
NDC: 52085-004 | Form: GAS
Manufacturer: Analgesic Services Inc
Category: prescription | Type: HUMAN PRESCRIPTION DRUG LABEL
Date: 20251029

ACTIVE INGREDIENTS: AIR 1000 mL/1 L

Medical Air

PACKAGE LABEL

AIR, COMPRESSED

UN1022

MEDICAL AIR, USP

Rx only. WARNING: Administration of Medical Air may be hazardous or contraindicated. For use only by or under the supervision of a licensed practitioner who is experienced in the use and administration of Medical Air and is familiar with the indications, effects, dosages, methods, and frequency and duration of administration, and with the hazards, contraindications and side effects, and the precautions to be taken.

WARNING: CONTAINS GAS UNDER PRESSURE; MAY EXPLODE IF HEATED. SUPPORTS COMBUSTION. Do not handle until all safety precautions have been read and understood. Use a back flow preventive device in the piping. Close valve after each use and when empty. Use only with equipment rated for cylinder pressure. Do not open valve until connected to equipment prepared for use. Protect from sunlight when ambient temperature exceeds 52 C (125 F). Read and follow the Safety Data Sheet (SDS) before use. CAS 132259-10-0 DO NOT REMOVE THIS PRODUCT LABEL.

ANALGESIC SERVICES, INC.

1718 N. MARKET BLVD, SUITE 300

SACRAMENTO, CA 95834 (888) 928-1068